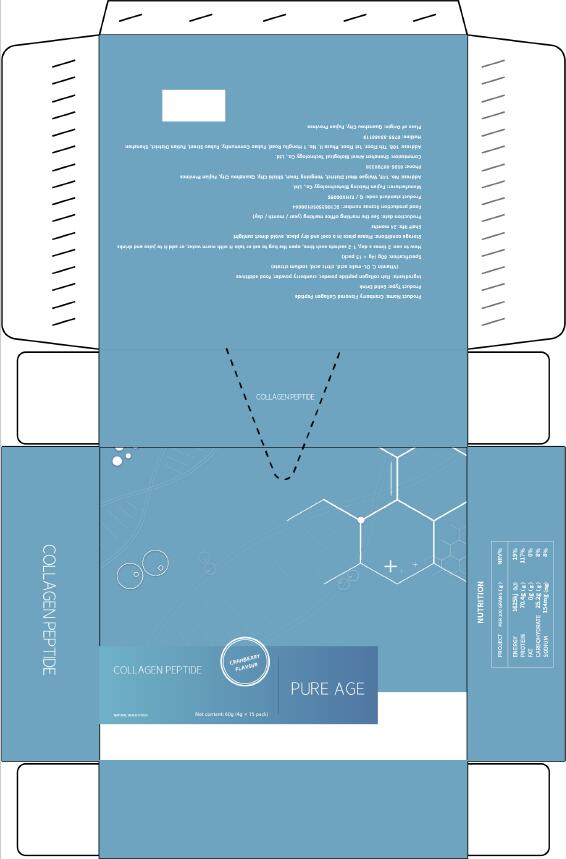 DRUG LABEL: COLLAGEN PEPTIDE
NDC: 55030-001 | Form: POWDER
Manufacturer: Shenzhen Aiwei Biological Technology Co., Ltd.
Category: homeopathic | Type: HUMAN OTC DRUG LABEL
Date: 20200603

ACTIVE INGREDIENTS: CRANBERRY 0.2 g/4 g; COLLAGEN, SOLUBLE, FISH SKIN 3 g/4 g
INACTIVE INGREDIENTS: ASCORBIC ACID; MALIC ACID; TRISODIUM CITRATE DIHYDRATE; CITRIC ACID MONOHYDRATE

DOSAGE AND ADMINISTRATION

4g/bag, 1 bag a day

WARNINGS

Please keep out of the reach of children

INACTIVE INGREDIENT

Vitamin C, DL-malic acid, citric acid, sodium citrate

INDICATIONS AND USAGE

: 2 times a day, 1-2 sachets each time, open the bag to eat or take it with warm water, or add it to juice and drinks

keep out of reach of children

PURPOSE

Replenish the protein needed by the body

ACTIVE INGREDIENT

Fish collagen peptide powder, cranberry powder